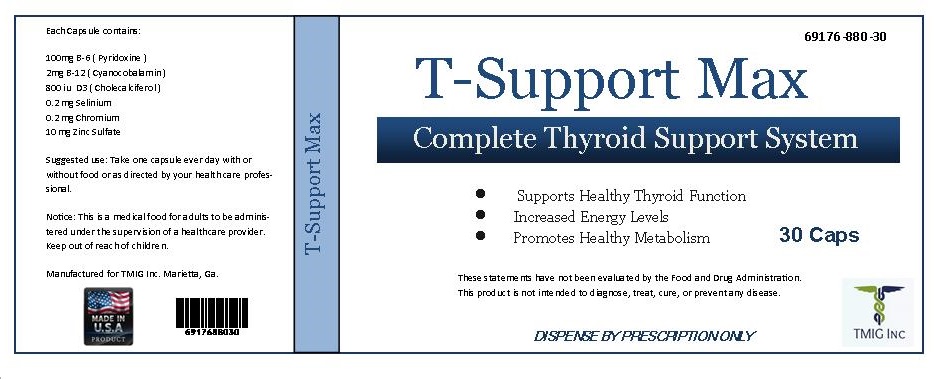 DRUG LABEL: T-Support Max
NDC: 69176-880 | Form: CAPSULE
Manufacturer: TMIG Inc.
Category: other | Type: MEDICAL FOOD
Date: 20170124

ACTIVE INGREDIENTS: FENAMIPHOS 100 mg/1 1; CHOLECALCIFEROL 800 [iU]/1 1; CYANOCOBALAMIN 2 mg/1 1; SELENIUM 0.2 mg/1 1; CHROMIUM 0.2 mg/1 1; ZINC SULFATE 10 mg/1 1
INACTIVE INGREDIENTS: GELATIN; MAGNESIUM STEARATE; BROWN RICE

T-Support Max - Complete Thyroid Support System

INDICATIONS AND USAGE

T-Support Max is indicated for the clinical dietary management of the individuals with Thyroid conditions.

Hyperthyroidism
Hyperthyroidism the name given to overproduction of thyrozine, causes extreme nervousness and irritability, increased heart rate and blood pressure, and weight loss. Underproduction of thyrozine, or hypothyroidism, results in dry skin, brittle nails, and a lack of energy in adults. Goiter, which is actually an enlarged thyroid, is a sign of thyroid insufficiency. In infants, hypothyroidism can be devastating, inhibiting physical development and causing irreversible mental retardation.

HypothyroidismHypothyroidism is a condition in which the thyroid gland fails to function adequately, resulting in reduced levels of thyroid hormone in the body. Cretinism is a type of hypothyroidism that occurs at birth and results in stunted physical growth and mental development. Severe hypothyroidism is called myxedema.

INTERACTIONS WITH DRUGS

Before using this product, tell your doctor or pharmacist of all the products you use. Keep a list of all
your medications with you, and share the list with your doctor and pharmacist. No decrease in
effectiveness of drugs has been reported with the use of T-Support Max

DESCRIPTION

T-Support Max is an orally-administered medical food dispensed by prescription for the clinical dietary
management of thyroid Use under medical supervision.

Keep out of reach of children. Pregnant or lactating women, those with thyroid disorders, and those undergoing treatment for a medical condition should consult a physician before taking this supplement.

Each capsule contains

100mg B-6 (Pyridoxine)
2mg B-12 (Cyanocobalamin)
800 iu D3 (Cholecalciferol)
0.2 mg Selinium
0.2 mg Chromium
10 mg Zinc Sulfate

The ingredients, indication or claims of this product are not to be construed to be drug claims. Statements in this document have not been evaluated by the Food and Drug Administration.This product is not intended to diagnose, treat, cure, or prevent disease.

WARNINGS AND PRECAUTIONS

T-Support Max capsules are used for the help of optimal function of the human thyroid. Should be used under medical supervision of you doctor or family physician. These capsules contain essential vitamins, minerals and amino acids involved in thyroid hormone synthesis.

PATIENT INFORMATION

T-Support Max is a prescription medical food to be used only under licensed medical supervision and
direction. Your licensed medical practitioner may choose to prescribe T-Suport Max along with other
medications .

STORAGE AND HANDLING

Store T-Support Max at controlled room temperature 15 C to 30 C (59 F to 86 F). Protect from light, heat and
moisture.

HOW SUPPLIED

T-Support Max is a is a medical food.

T-Support Max comes in bottles of 30 capsules.
T-Support Max Product Code is 69176-880-30

T-Support Max does not represent these product codes to be National Drug Codes (NDC). Product codes are
formatted according to standard industry practice, to meet the formatting requirements of pharmacy and
health insurance computer systems, and standard UPC bar codes.